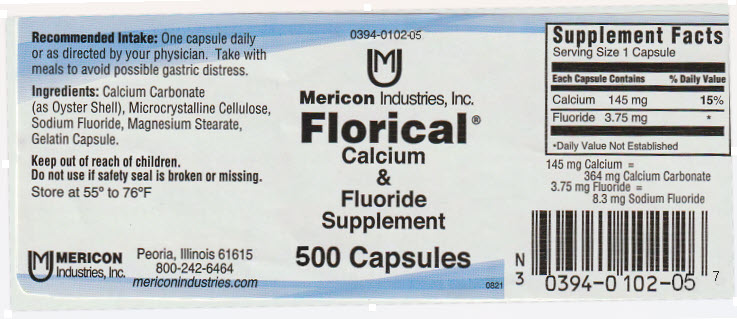 DRUG LABEL: Florical
NDC: 0394-0102 | Form: CAPSULE
Manufacturer: Mericon Industries
Category: other | Type: DIETARY SUPPLEMENT
Date: 20250115

ACTIVE INGREDIENTS: Sodium Fluoride 8.3 mg/1 1; Calcium Carbonate 364 mg/1 1
INACTIVE INGREDIENTS: MICROCRYSTALLINE CELLULOSE; MAGNESIUM STEARATE; GELATIN, UNSPECIFIED

Florical®

Recommended Intake

One capsule daily or as directed by your physician. Take with meals to avoid possible gastric distress.

Ingredients

Calcium Carbonate (as Oyster Shell), Microcrystalline Cellulose, Sodium Fluoride, Magnesium Stearate, Gelatin Capsule.

Keep out of reach of children.

Do not use if safety seal is broken or missing.

Store at 55° to 76°F

STATEMENT OF IDENTITY

Supplement Facts

Serving Size 1 Capsule

Each Capsule Contains

% Daily Value

Calcium

145 mg

15%

Fluoride

3.75 mg

[Daily Value Not Established]

145 mg Calcium =
364 mg Calcium Carbonate

3.75 mg Fluoride =
8.3 mg Sodium Fluoride

HEALTH CLAIM

MERICON
Industries, Inc.

Peoria, Illinois 61615
800-242-6464
mericonindustries.com

PRINCIPAL DISPLAY PANEL - 500 Capsule Bottle Label

0394-0102-05

Mericon Industries, Inc.

Florical®
Calcium
&
Fluoride
Supplement

500 Capsules

0821